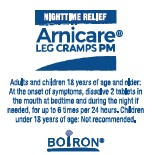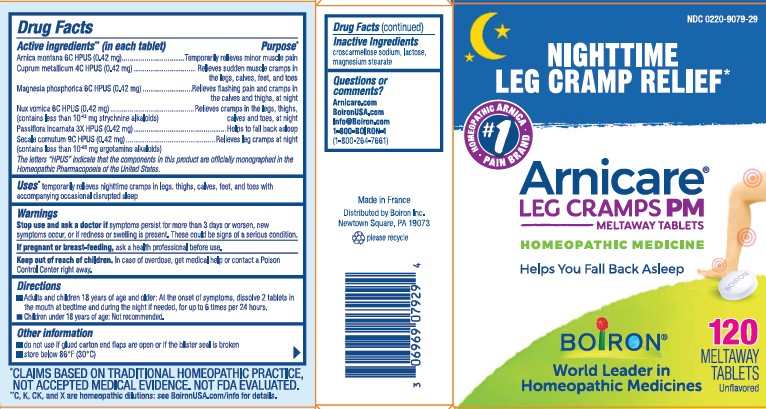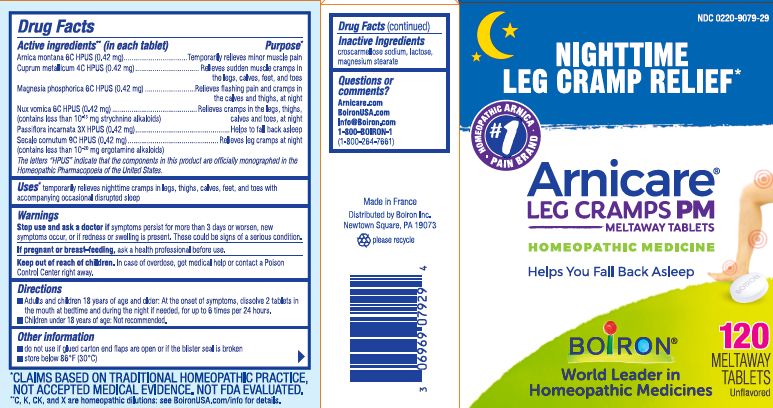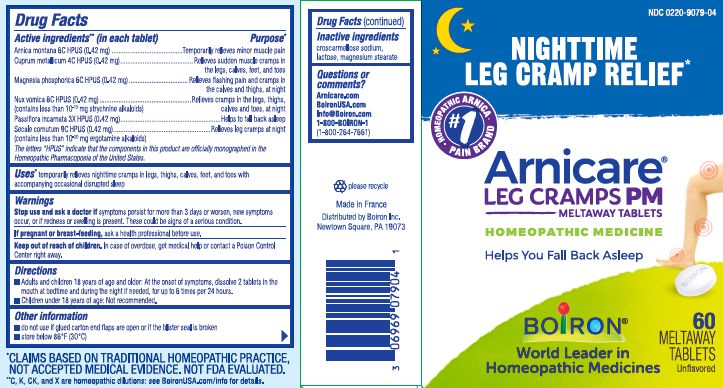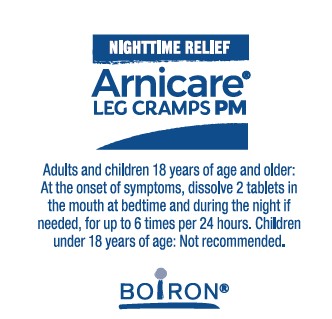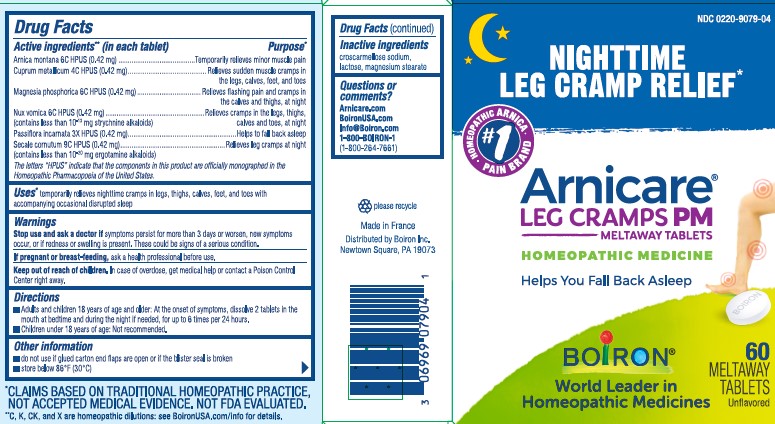 DRUG LABEL: Arnicare Leg Cramps
NDC: 0220-9079 | Form: TABLET
Manufacturer: Laboratoires Boiron
Category: homeopathic | Type: HUMAN OTC DRUG LABEL
Date: 20240701

ACTIVE INGREDIENTS: PASSIFLORA INCARNATA TOP 3 [hp_X]/1 1; COPPER 4 [hp_C]/1 1; ARNICA MONTANA 6 [hp_C]/1 1; MAGNESIUM PHOSPHATE, DIBASIC TRIHYDRATE 6 [hp_C]/1 1; STRYCHNOS NUX-VOMICA SEED 6 [hp_C]/1 1; CLAVICEPS PURPUREA SCLEROTIUM 9 [hp_C]/1 1
INACTIVE INGREDIENTS: MAGNESIUM STEARATE; CROSCARMELLOSE SODIUM; LACTOSE, UNSPECIFIED FORM

Arnicare Leg Cramps PM

Active ingredients** (in each tablet)

Arnica montana 6C HPUS (0.42 mg)

Cuprum metallicum 4C HPUS (0.42 mg)

Magnesia phosphorica 6C HPUS (0.42 mg)

Nux vomica 6C HPUS (0.42 mg) (contains less than 10^-13 mg strychnine alkaloids)

Passiflora incarnata 3X HPUS (0.42 mg)

Secale cornutum 9C HPUS (0.42 mg) (contains less thank 10^-20 mg ergotamine alkaloids)

The letters "HPUS" indicate that the components in this product are officially monographed in the Homeopathic Pharmacopoeia of the United States.

Purpose*

Arnica montana 6C HPUS ... Temporarily relieves minor muscle pain

Cuprum metallicum 4C HPUS ... Relieves sudden muscle cramps in the legs, calves, feet, and toes

Magnesia phosphorica 6C HPUS ... Relieves flashing pain and cramps in the calves and thighs, at night

Nux vomica 6C HPUS ... Relieves cramps in the legs, thighs, calves and toes, at night

Passiflora incarnata 3X HPUS ... Helps to fall back asleep

Secale cornutum 9C HPUS ... Relieves leg cramps at night

INDICATIONS AND USAGE

Uses* temporarily relieves nighttime cramps in legs, thighs, calves, feet, and toes with accompanying occasional disrupted sleep

Stop use and ask a doctor if symptoms persist for more than 3 days or worsen, new symptoms occur, or if redness or swelling is present. These could be signs of a serious condition.

PREGNANCY OR BREAST FEEDING

If pregnant or breast-feeding, ask a health professional before use.

Keep out of reach of children. In case of overdose, get medical help or contact a Poison Control Center right away.

DOSAGE AND ADMINISTRATION

- Adults and children 18 years of age and older: At the onset of symptoms, dissolve 2 tablets in the mouth at bedtime and during the night if needed, for up to 6 times per 24 hours.
- Children under 18 years of age: Not recommended.

INACTIVE INGREDIENT

croscarmellose sodium, lactose, magnesium stearate

Questions or comments?

Arnicare.com

BoironUSA.com

Info@Boiron.com

1-800-BOIRON-1

(1-800-264-7661)

Made in France

Distributed by Boiron, Inc.

Newtown Square, PA 19073

do not use if glued carton end flaps are open or if the blister seal is broken

store below 86oF (30oC)

60 Meltaway Tablets, unflavored

120 Meltaway Tablets, unflavored

Nighttime Leg Cramp Relief*

Plant-Based & Other Pure Actives

Non-Habit Forming

No Known Drug Interactions

No Artificial Sweeteners, Flavors, Colors or Preservatives

*CLAIMS BASED ON TRADITIONAL HOMEOPATHIC PRACTICE NOT ACCEPTED MEDICAL EVIDENCE. NOT FDA EVALUATED.
**C,K,CK, and X are homeopathic dilutions: see BoironUSA.com/info for details.